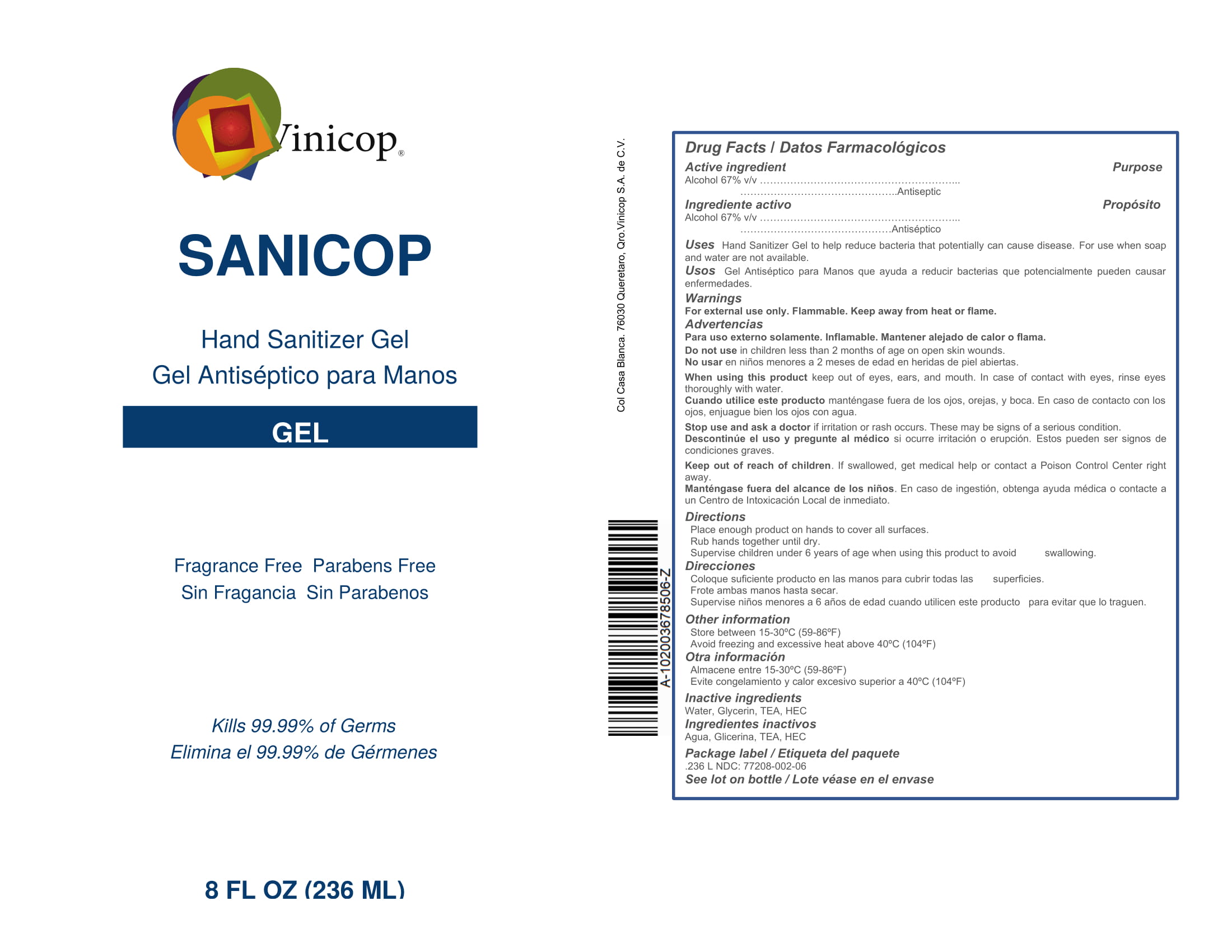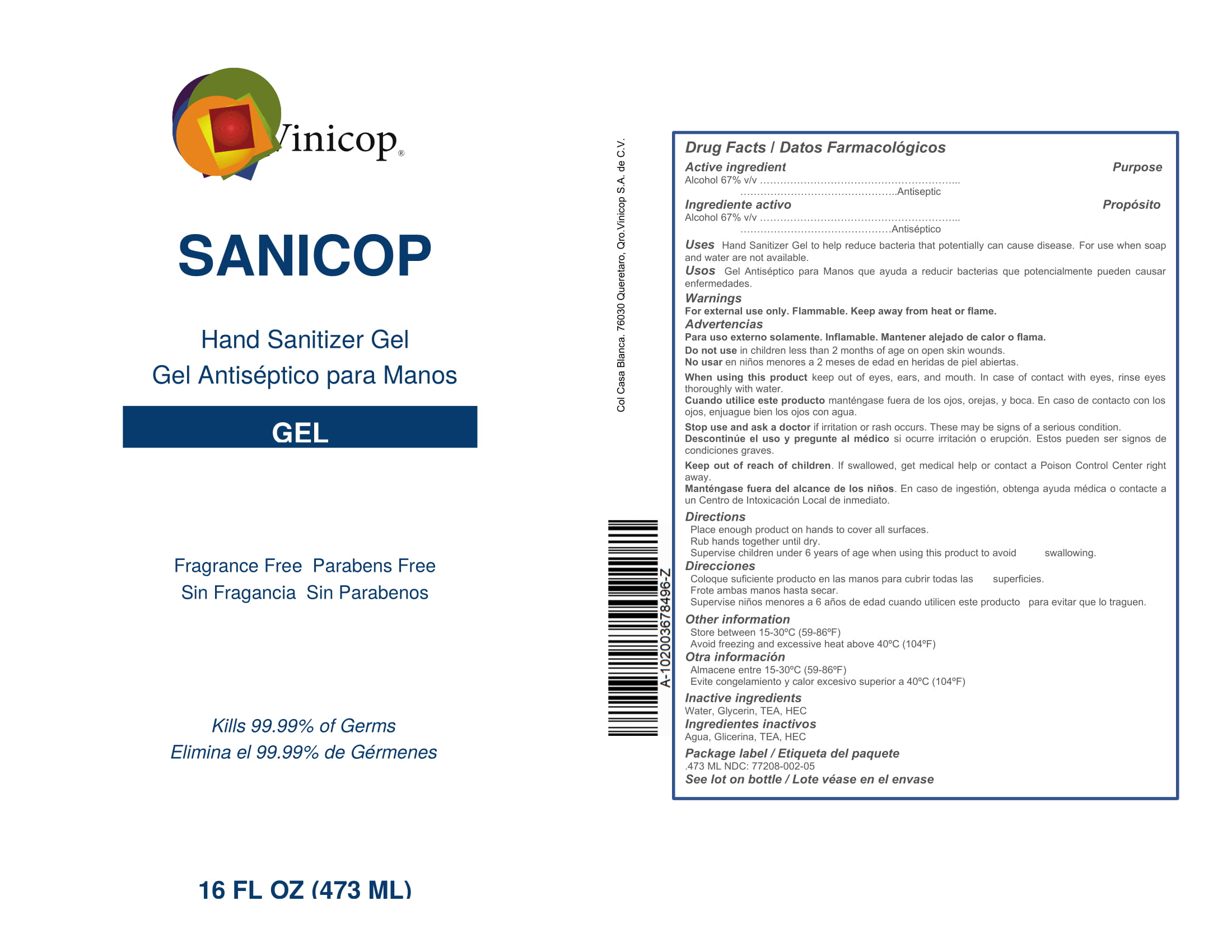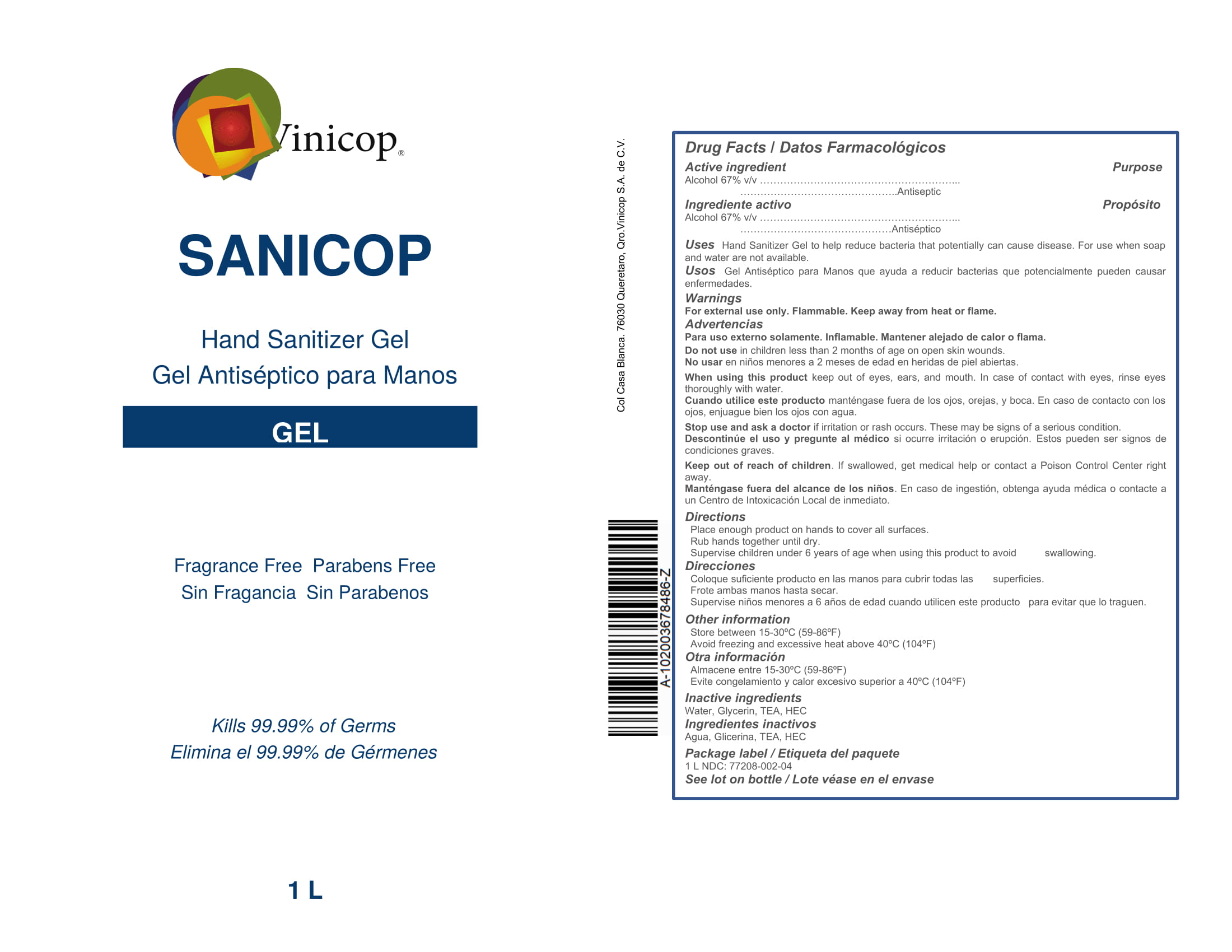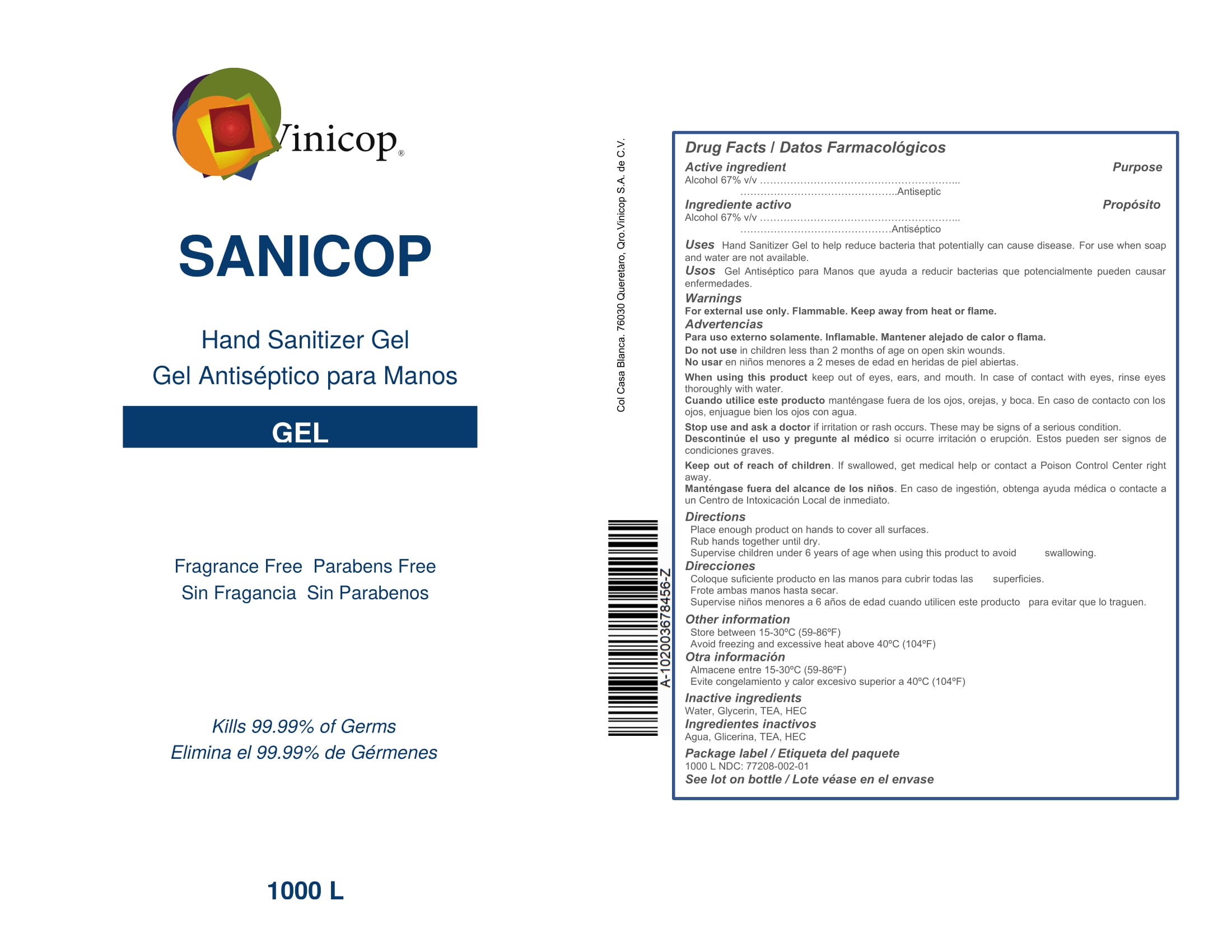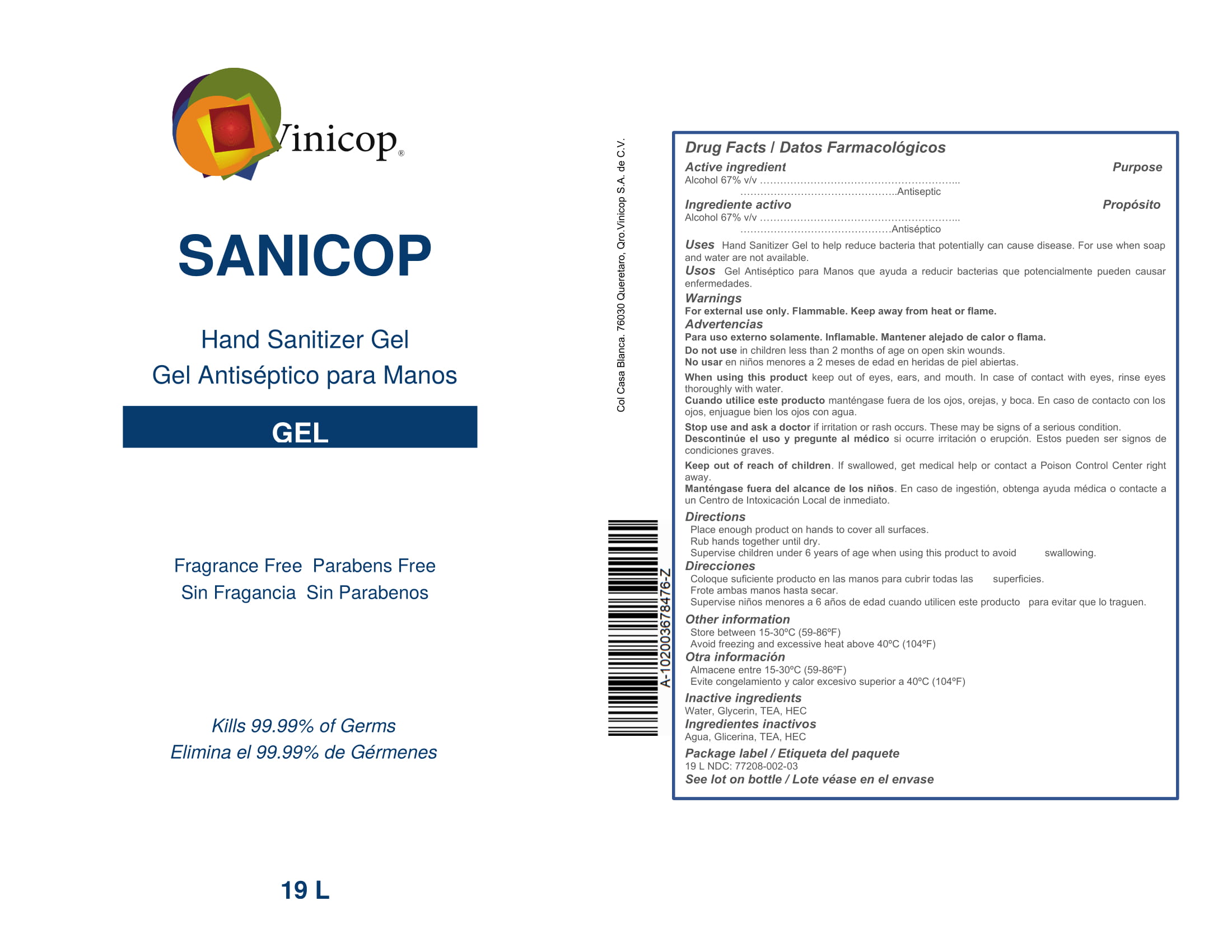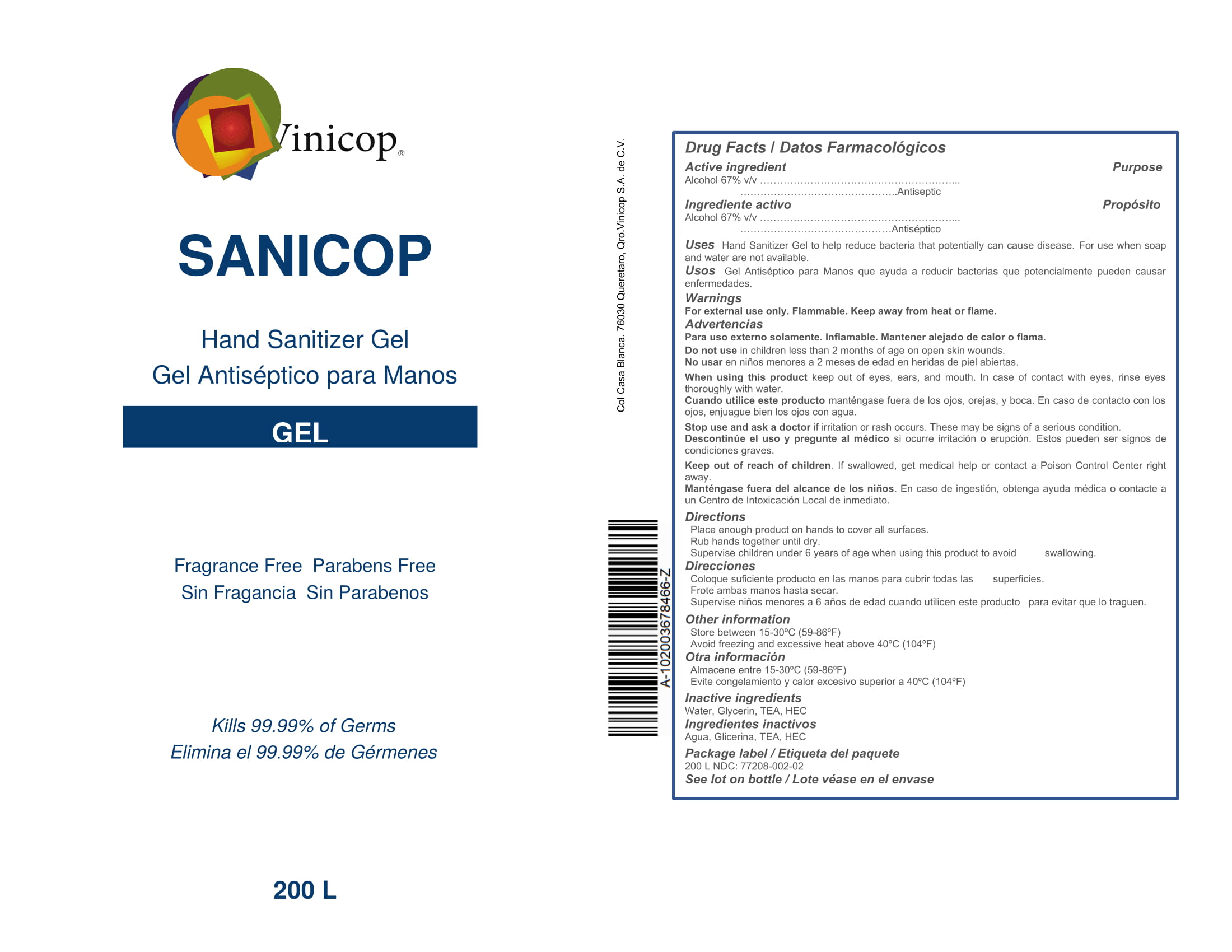 DRUG LABEL: SANICOP HAND SANITIZER
NDC: 77208-002 | Form: GEL
Manufacturer: vinicop s.a. de c.v.
Category: otc | Type: HUMAN OTC DRUG LABEL
Date: 20200604

ACTIVE INGREDIENTS: ALCOHOL 67 L/67 L
INACTIVE INGREDIENTS: TROLAMINE; HYDROXYETHYL ETHYLCELLULOSE; GLYCERIN; WATER

ACTIVE INGREDIENT

Alcohol 67% v/v. Purpose: Antiseptic

PURPOSE

Antiseptic, Hand Sanitizer

INDICATIONS AND USAGE

Hand Sanitizer to help reduce bacteria that potentially can cause disease. For use when soap and water are not available.

WARNINGS

For external use only. Flammable. Keep away from heat or flame

Do not use:

· in children less than 2 months of age

· on open skin wounds

When using this product keep out of eyes, ears, and mouth. In case of contact with eyes, rinse eyes thoroughly with water.

Stop use and ask a doctor if irritation or rash occurs. These may be signs of a serious condition.

Keep out of reach of children. If swallowed, get medical help or contact a Poison Control Center right away.

DOSAGE AND ADMINISTRATION

· Place enough product on hands to cover all surfaces. Rub hands together until dry.

· Supervise children under 6 years of age when using this product to avoid swallowing.

STORAGE AND HANDLING

· Store between 15-30ºC (59-86ºF)

· Avoid freezing and excessive heat above 40ºC (104ºF)

INACTIVE INGREDIENT

Glyceryn, Water, TEA, HEC

PACKAGE LABEL

.236 L NDC: 77208-002-06

.473 L NDC: 77208-002-05

1 L NDC: 77208-002-04

19 L NDC: 77208-002-03

200 L NDC: 77208-002-02

1000 L NDC: 77208-002-01